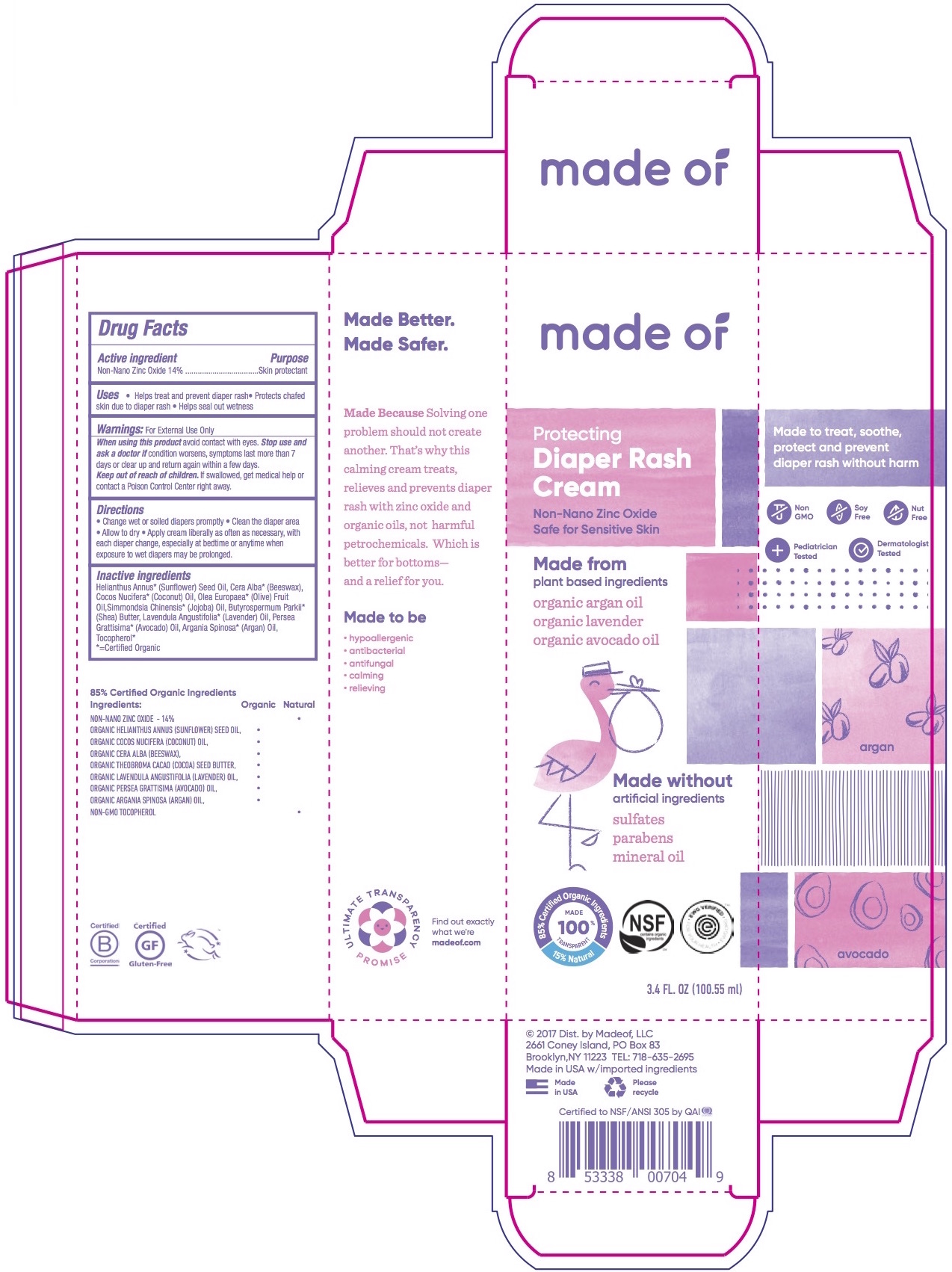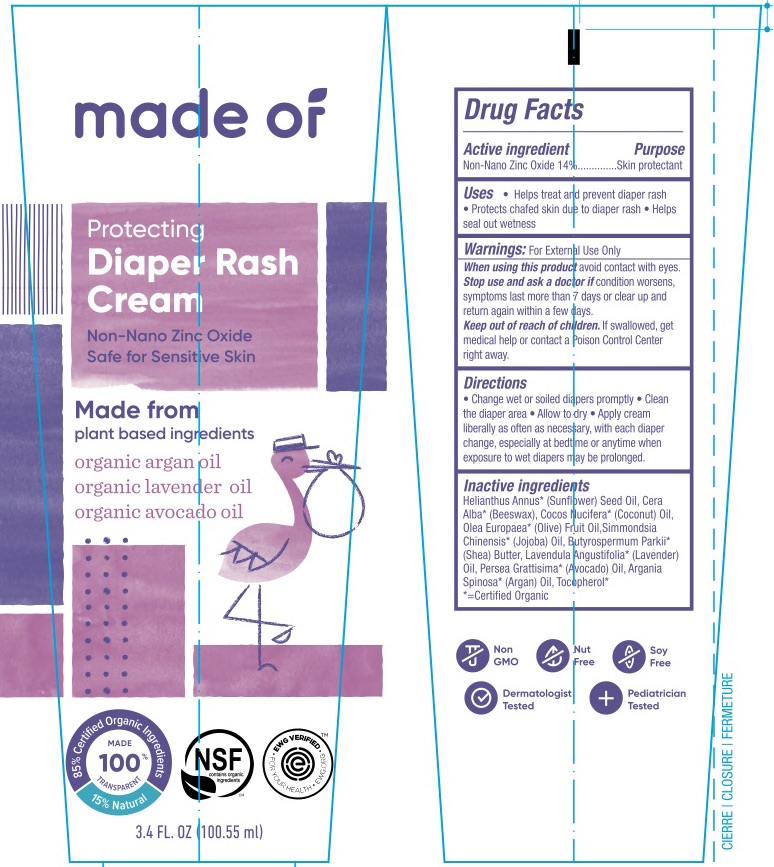 DRUG LABEL: made of Diaper Rash Cream
NDC: 71439-040 | Form: CREAM
Manufacturer: MADEOF, LLC
Category: otc | Type: HUMAN OTC DRUG LABEL
Date: 20200117

ACTIVE INGREDIENTS: ZINC OXIDE 14 g/100 mL
INACTIVE INGREDIENTS: SUNFLOWER OIL; YELLOW WAX; TOCOPHEROL; LAVENDER OIL; SHEA BUTTER; AVOCADO OIL; ARGAN OIL; OLIVE OIL; COCONUT OIL; JOJOBA OIL

made of® Diaper Rash Cream

Drug Facts

Active Ingredient

USP Zinc Oxide 14%

Purpose

Skin Protectant

Uses

- Helps prevent and treat diaper rash
- Protects chafed skin due to diaper rash
- Helps seal out wetness

Warnings

For external use only

When using this product

avoid contact with eyes.

Stop use and ask a doctor if

condition worsens, symptoms last more than 7 days or clear up and return again within a few days.

Keep out of reach of children. If swallowed, get medical help or contact a poison control center right away.

Directions

- Change wet or soiled diapers promptly
- Clean the diaper area
- Allow to dry
- Apply cream liberally as often as necessary, with each diaper change, especially at bedtime or anytime when exposure to wet diapers may be prolonged.

Ingredients

[= Certified Organic] Helianthus Annus* (Sunflower) Seed Oil, Cera Alba* (Beeswax), Cocos Nucifera* (Coconut) Oil, Olea Europaea' (Olive) Fruit Oil, Simmondsia Chinensis* (Jojoba) Oil, Butyrospermum Parkii* (Shea) Butter, Lavendula Angustilolia* (Lavender) Oil, Persea Grattisima*(Avocado) Oil, Argania Spinosa* (Argan) Oil, Tocopherol*

.

PRINCIPAL DISPLAY PANEL - 100.55 ml Box and Tube Label

made of®

Diaper Rash Cream

85% Certified Organic Ingredients

15% Natural

NSF
EWG VERIFIED
Non GMO

Nut Free

Soy Free

Dermatologist Tested

Pediatrician Tested

3.4 fl.oz (100.55ml)